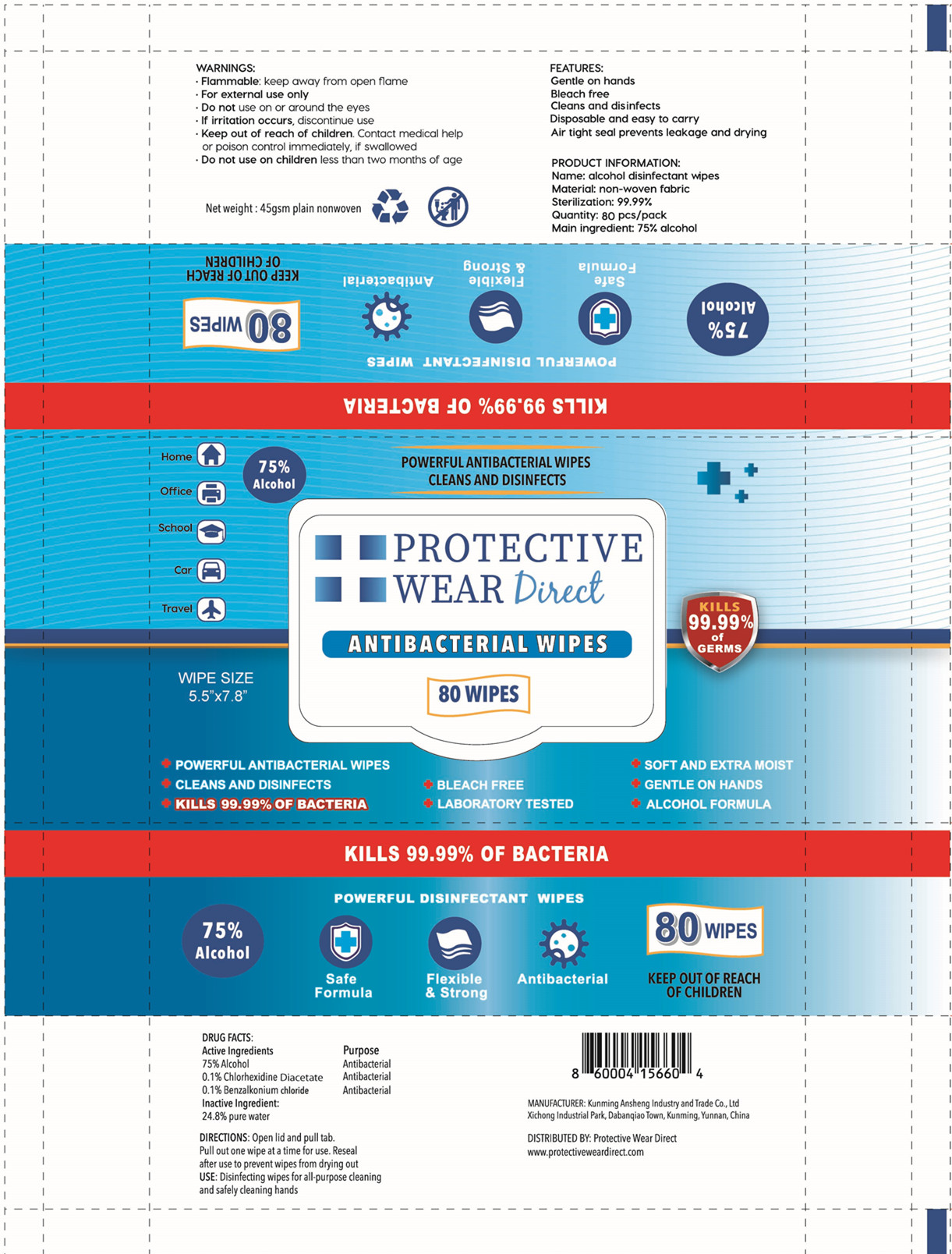 DRUG LABEL: alcohol disinfectant wipes
NDC: 78183-008 | Form: CLOTH
Manufacturer: Kunming Ansheng Industry & Trade Co., Ltd.
Category: otc | Type: HUMAN OTC DRUG LABEL
Date: 20200624

ACTIVE INGREDIENTS: ALCOHOL 750 mg/1 1; BENZALKONIUM CHLORIDE 1 mg/1 1; CHLORHEXIDINE ACETATE 1 mg/1 1
INACTIVE INGREDIENTS: WATER

ACTIVE INGREDIENT

75% alcohol

0.1% chlorhexidine diacetate

0.1% benzalkonium chloride

PURPOSE

Antibacterial

Antibacterial

Antibacterial

INACTIVE INGREDIENT

24.8% pure water

DIRECTIONS

Open lid and pull tab.

Pull out one wipe at a time for use.

Reseal after use to prevent wipes from drying out.

USE

Disinfecting wipes for all-purpose cleaning and safety cleaning hands.

WARNINGS

- Flammable: keep away from open flame
- For external use only.
- Do not use on or around the eyes.
- If irritation occurs, discontinue use

Keep out of reach of children. Contact medical help or poison control immediately,if swallowed
Do not use on children less than two months of age.